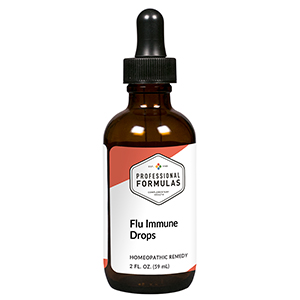 DRUG LABEL: Flu Immune Drops
NDC: 63083-2145 | Form: LIQUID
Manufacturer: Professional Complementary Health Formulas
Category: homeopathic | Type: HUMAN OTC DRUG LABEL
Date: 20190815

ACTIVE INGREDIENTS: ECHINACEA PURPUREA WHOLE 3 [hp_X]/59 mL; ACONITUM NAPELLUS WHOLE 6 [hp_X]/59 mL; AMARYLLIS BELLADONNA WHOLE 6 [hp_X]/59 mL; BRYONIA ALBA ROOT 6 [hp_X]/59 mL; PULSATILLA MONTANA WHOLE 6 [hp_X]/59 mL; SULFUR 6 [hp_X]/59 mL; GELSEMIUM SEMPERVIRENS ROOT 6 [hp_X]/59 mL; CAIRINA MOSCHATA HEART/LIVER AUTOLYSATE 200 [hp_X]/59 mL
INACTIVE INGREDIENTS: ALCOHOL; WATER

C145

ACTIVE INGREDIENTS

Echinacea purpurea 3X
Aconitum napellus 6X, 12X, 30X
Belladonna 6X, 12X, 30X
Bryonia 6X, 12X, 30X
Pulsatilla 6X, 12X, 30X
Sulphur 6X, 12X, 30X
Gelsemium sempervirens 6X, 12X, 30X
Anas barbariae hepatis 200C

QUESTIONS

Professional Formulas

PO Box 2034 Lake Oswego, OR 97035

INDICATIONS

For the temporary relief of congestion, runny nose, muscle aches, low-grade fever, or occasional headache.*

PURPOSE

*Claims based on traditional homeopathic practice, not accepted medical evidence. Not FDA evaluated.

WARNINGS

Persistent symptoms may be a sign of a serious condition. If symptoms persist or are accompanied by a fever, rash, or persistent headache, consult a doctor. Keep out of the reach of children. In case of overdose, get medical help or contact a poison control center right away. If pregnant or breastfeeding, ask a healthcare professional before use.

Keep out of the reach of children.

PREGNANCY OR BREAST FEEDING

If pregnant or breastfeeding, ask a healthcare professional before use.

DIRECTIONS

Place drops under tongue 30 minutes before/after meals. Adults and children 12 years and over: Take 10 drops up to 3 times per day for up to 6 weeks. For immediate onset of symptoms, take 10 to 15 drops every 15 minutes up to 3 hours. For less severe symptoms, take 10-15 drops hourly up to 8 hours. Consult a physician for use in children under 12 years of age.

OTHER INFORMATION

Tamper resistant. If seal is broken, do not use. After opening, close container tightly and store at room temperature away from heat.

INACTIVE INGREDIENTS

20% ethanol, purified water.

LABEL

Est 1985

Professional Formulas

Complementary Health

Flu Immune Drops

Homeopathic Remedy

2 FL. OZ. (59 mL)